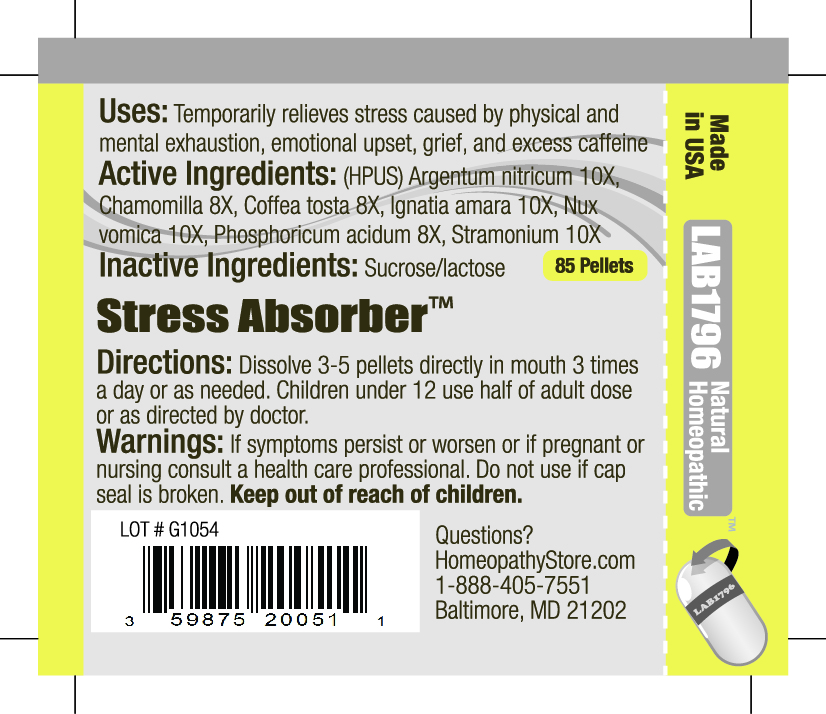 DRUG LABEL: Lab1796 Stress Absorber
NDC: 59875-2005 | Form: PELLET
Manufacturer: HomeopathyStore.com
Category: homeopathic | Type: HUMAN OTC DRUG LABEL
Date: 20101230

ACTIVE INGREDIENTS: STRYCHNOS NUX-VOMICA SEED 10 [hp_X]/1 1; SILVER NITRATE 10 [hp_X]/1 1; DATURA STRAMONIUM 10 [hp_X]/1 1; STRYCHNOS IGNATII SEED 10 [hp_X]/1 1; PHOSPHORIC ACID 8 [hp_X]/1 1; MATRICARIA RECUTITA 8 [hp_X]/1 1; COFFEE BEAN 8 [hp_X]/1 1
INACTIVE INGREDIENTS: SUCROSE; LACTOSE

Stress Absorber

Uses:

Temporarily relieves stress caused by physical and mental exhaustion, emotional upset, grief, and excess caffeine

Active Ingredients:

(HPUS) Argentum nitricum 10X, Chamomilla 8X, Coffea tosta 8X, Ignatia amara 10X, Nux vomica 10X, Phosphoricum acidum 8X, Stramonium 10X

Inactive Ingredients:

Sucrose/lactose

Directions:

DOSAGE AND ADMINISTRATION

Dissolve 3-5 pellets directly in mouth 3 times a day or as needed. Children under 12 use half of adult dose or as directed by doctor.

Warnings:

If symptoms persist or worsen or if pregnant or nursing consult a health care professional. Do not use if cap seal is broken.

Keep out of reach of children.